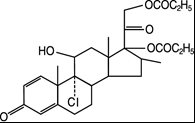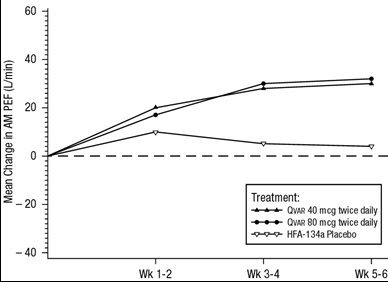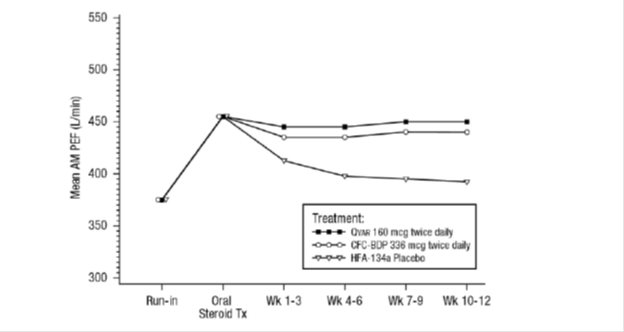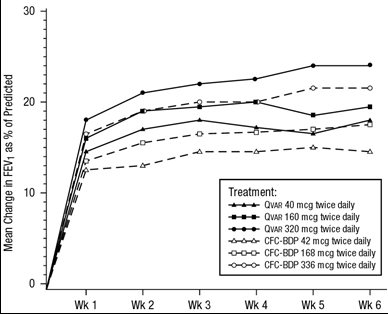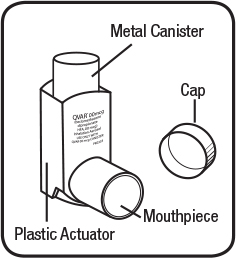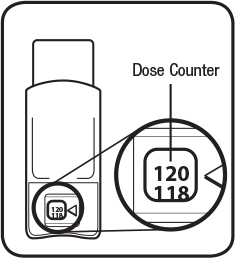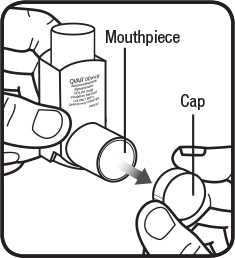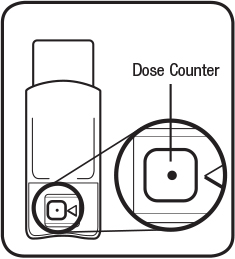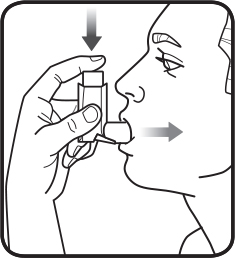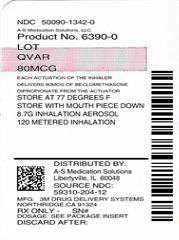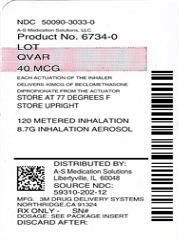 DRUG LABEL: QVAR
NDC: 50090-1342 | Form: AEROSOL, METERED
Manufacturer: A-S Medication Solutions
Category: prescription | Type: HUMAN PRESCRIPTION DRUG LABEL
Date: 20180831

ACTIVE INGREDIENTS: BECLOMETHASONE DIPROPIONATE 80 ug/1 1
INACTIVE INGREDIENTS: NORFLURANE; ALCOHOL

HIGHLIGHTS OF PRESCRIBING INFORMATION

These highlights do not include all the information needed to use QVAR safely and effectively. See full prescribing information for QVAR Inhalation Aerosol.
QVAR® (beclomethasone dipropionate HFA), inhalation aerosol, for oral inhalation use
Initial U.S. Approval: 1976

RECENT MAJOR CHANGES

Indications and Usage (1) 09/2017

Dosage and Administration (2.1,2.2) 09/2017

Warnings and Precautions (5.10) 09/2017

1 INDICATIONS AND USAGE

QVAR is a corticosteroid indicated for:

- Maintenance treatment of asthma as prophylactic therapy in patients 5 years of age and older. (1)

Important Limitations:

- Not indicated for the relief of acute bronchospasm. (1)

2 DOSAGE AND ADMINISTRATION

For oral inhalation only. (2.1)

- Starting dosage is based on prior asthma therapy and disease severity. (2.2)
- Treatment of asthma in patients 12 years and older: 40 mcg, 80 mcg, 160 mcg, or 320 mcg twice daily.(2.2)
- Treatment of asthma in patients 5 to 11 years of age: 40 or 80 mcg twice daily. (2.2)
- Discard QVAR inhaler when the dose counter displays 0 or after the expiration date on the product, whichever comes first. (2.1)

3 DOSAGE FORMS AND STRENGTHS

- Inhalation aerosol: 40 or 80 mcg per actuation (3)

4 CONTRAINDICATIONS

- Primary treatment of status asthmaticus or other acute episodes of asthma where intensive measures are required. (4)
- Hypersensitivity to any of the ingredients of QVAR. (4)

5 WARNINGS AND PRECAUTIONS

- Localized infections: Candida albicans infection of the mouth and throat may occur. Monitor patients periodically for signs of adverse effects on the oral cavity. Advise patients to rinse the mouth with water without swallowing after inhalation. (5.1)
- Deterioration of asthma and acute episodes: Do not use QVAR for relief of acute symptoms. Patients require immediate re-evaluation during rapidly deteriorating asthma. (5.2)
- Transferring patients from systemic corticosteroids: Risk of impaired adrenal function when transferring from oral steroids. Taper patients slowly from systemic corticosteroids if transferring to QVAR. (5.3)
- Immunosuppression: Potential worsening of existing tuberculosis, fungal, bacterial, viral, or parasitic infection; or ocular herpes simplex infections. More serious or even fatal course of chickenpox or measles can occur in susceptible patients. Use with caution in patients with these infections because of the potential for worsening of these infections. (5.4)
- Paradoxical Bronchospasm: Bronchospasm, with an immediate increase in wheezing, may occur after dosing. Treat bronchospasm immediately with inhaled, short-acting bronchodilator and discontinue QVAR. (5.5)
- Hypersensitivity Reactions: Hypersensitivity reactions, such as urticaria, angioedema, rash, and bronchospasm may occur. Discontinue QVAR if such reactions occur. (5.6)
- Hypercorticism and adrenal suppression: May occur with very high dosages or at the regular dosage in susceptible individuals. If such changes occur, discontinue QVAR slowly. (5.7)
- Effects on growth: Monitor growth of pediatric patients. (5.8)
- Decreases in bone mineral density: Monitor patients with major risk factors for decreased bone mineral content. (5.9)
- Eye Disorders: Monitor patients with change in vision or with a history of increased intraocular pressure, blurred vision, glaucoma, and/or cataracts closely. (5.10)

6 ADVERSE REACTIONS

Most common adverse reactions (incidence >3% and > placebo) include headache, pharyngitis, oral symptoms (inhalation route), and sinusitis. (6.1)

To report SUSPECTED ADVERSE REACTIONS, contact Teva Respiratory, LLC at 1-888-482-9522 or FDA at 1-800-FDA-1088 or www.fda.gov/medwatch.

FULL PRESCRIBING INFORMATION

1 INDICATIONS AND USAGE

QVAR® is indicated in the maintenance treatment of asthma as prophylactic therapy in patients 5 years of age and older.

Important Limitations of Use:

- QVAR is NOT indicated for the relief of acute bronchospasm.

2 DOSAGE AND ADMINISTRATION

2.1 Administration Information

Administer QVAR by the orally inhaled route in patients 5 years of age and older. QVAR does not require shaking prior to use. After inhalation, the patient should rinse his/her mouth with water without swallowing to help reduce the risk of oropharyngeal candidiasis.

Use of QVAR with a spacer device in children less than 5 years of age is not recommended. [see Use in Specific Populations (8.4)]

Patients should be instructed on the proper use of their inhaler. Consistent dose delivery is achieved, whether using the 40 or 80 mcg strengths, due to proportionality of the 2 products (i.e., 2 actuations of 40 mcg strength should provide a dose comparable to 1 actuation of the 80 mcg strength).

Priming: Patients should prime QVAR by actuating into the air twice before using for the first time or if QVAR has not been used for over 10 days. Avoid spraying in the eyes or face when priming QVAR.

Dose Counter: QVAR has a dose counter attached to the actuator. When the patient receives the inhaler, a black dot will appear in the viewing window until it has been primed 2 times, at which point the total number of actuations will be displayed. The dose counter will count down each time a spray is released. The dose-counter window displays the number of sprays left in the inhaler in units of two (e.g., 120, 118, 116, etc). When the dose counter reaches 20, the color of the numbers will change to red to remind the patient to contact their pharmacist for a refill of medication or consult their physician for a prescription refill. When the dose counter reaches 0, the background will change to solid red.

Discard QVAR inhaler when the dose counter displays 0 or after the expiration date on the product, whichever comes first.

2.2 Recommended Dosage

Adults and Adolescents 12 years of age and older

The starting dosage is based on previous asthma therapy and disease severity, including consideration of the patients’ current control of asthma symptoms and risk of future exacerbation. The recommended starting dosage for patients 12 years of age and older who are not on an inhaled corticosteroid is 40 to 80 mcg twice daily, approximately 12 hours apart. For patients switching to QVAR from another inhaled corticosteroid product, select the appropriate starting dosage strength of QVAR based on the strength of the previous inhaled corticosteroid product and disease severity: 40, 80, 160 or 320 mcg twice daily. For patients who do not respond adequately to the initial dosage after 2 weeks of therapy, increasing the dosage may provide additional asthma control. The maximum recommended dosage for patients 12 years of age and older is 320 mcg twice daily.

Pediatric Patients 5 to 11 years

The starting dosage is based on previous asthma therapy and disease severity, including consideration of the patients’ current control of asthma symptoms and risk of future exacerbation. The recommended starting dosage for patients aged 5 to 11 years of age is 40 mcg twice daily, approximately 12 hours apart. For patients who do not respond adequately to QVAR 40 mcg after 2 weeks of therapy, increasing the dosage to QVAR 80 mcg twice daily may provide additional asthma control. The maximum recommended dosage for patients 5 to 11 years of age is 80 mcg twice daily.

General Dosing Recommendations

The onset and degree of symptom relief will vary in individual patients. Improvement in asthma symptoms can occur within 24 hours of the beginning of treatment and should be expected within the first or second week, but maximum benefit should not be expected until 3 to 4 weeks of therapy. Improvement in pulmonary function is usually apparent within 1 to 4 weeks after the start of therapy.

If a dosage regimen of QVAR fails to provide adequate control of asthma, the therapeutic regimen should be re-evaluated and additional therapeutic options (e.g., replacing the current strength of QVAR with a higher strength, or adding additional controller therapies) should be considered.

As with any inhaled corticosteroid, physicians are advised to titrate the dose of QVAR downward over time to the lowest level that maintains proper asthma control. This is particularly important in children since a controlled study has shown that QVAR has the potential to affect growth in children.

3 DOSAGE FORMS AND STRENGTHS

Inhalation Aerosol: QVAR is a pressurized, metered-dose aerosol with a dose counter intended for oral inhalation containing beclomethasone dipropionate in the following 2 strengths:

QVAR 40 mcg is supplied in an aluminum canister with a beige plastic actuator with a dose counter and a gray dust cap. Each actuation delivers 50 mcg of beclomethasone dipropionate from the valve and 40 mcg from the actuator. QVAR 40 mcg is available as a 120-inhalation/8.7 g canister.

QVAR 80 mcg is supplied in an aluminum canister with a dark mauve plastic actuator with a dose counter and a gray dust cap. Each actuation delivers 100 mcg of beclomethasone dipropionate from the valve and 80 mcg from the actuator. QVAR 80 mcg is available as a 120-inhalation/8.7 g canister.

4 CONTRAINDICATIONS

4.1 Status Asthmaticus

QVAR is contraindicated in the primary treatment of status asthmaticus or other acute episodes of asthma where intensive measures are required.

4.2 Hypersensitivity

QVAR is contraindicated in patients with known hypersensitivity to beclomethasone dipropionate or any of the ingredients in QVAR [see Warnings and Precautions (5.6)].

5 WARNINGS AND PRECAUTIONS

5.1 Local Effects

Localized infections with Candida albicans have occurred in the mouth and pharynx in some patients receiving QVAR. If oropharyngeal candidiasis develops, it should be treated with appropriate local or systemic (i.e., oral) antifungal therapy while still continuing with QVAR therapy, but at times therapy with QVAR may need to be temporarily interrupted under close medical supervision. Rinsing the mouth with water without swallowing after inhalation is advised.

5.2 Deterioration of Asthma and Acute Episodes

QVAR is not indicated for the relief of acute symptoms, i.e., as rescue therapy for the treatment of acute episodes of bronchospasm. An inhaled, short-acting beta-2 agonist, not QVAR, should be used to relieve acute symptoms such as shortness of breath. Instruct patients to contact their physician immediately if episodes of asthma that are not responsive to bronchodilators occur during the course of treatment with QVAR. During such episodes, patients may require therapy with oral corticosteroids.

5.3 Transferring Patients from Systemic Corticosteroid Therapy

Particular care is needed in patients who are transferred from systemically active corticosteroids to QVAR because deaths due to adrenal insufficiency have occurred in asthmatic patients during and after transfer from systemic corticosteroids to less systemically available inhaled corticosteroids. After withdrawal from systemic corticosteroids, a number of months are required for recovery of hypothalamic-pituitary-adrenal (HPA) function.

Patients who have been previously maintained on 20 mg or more per day of prednisone (or its equivalent) may be most susceptible, particularly when their systemic corticosteroids have been almost completely withdrawn. During this period of HPA suppression, patients may exhibit signs and symptoms of adrenal insufficiency when exposed to trauma, surgery, or infections (particularly gastroenteritis) or other conditions with severe electrolyte loss. Although QVAR may provide control of asthmatic symptoms during these episodes, in recommended doses it supplies less than normal physiological amounts of glucocorticoid systemically and does NOT provide the mineralocorticoid that is necessary for coping with these emergencies.

During periods of stress or a severe asthmatic attack, patients who have been withdrawn from systemic corticosteroids should be instructed to resume oral corticosteroids (in large doses) immediately and to contact their physician for further instruction. These patients should also be instructed to carry a warning card indicating that they may need supplementary systemic steroids during periods of stress or a severe asthma attack.

Patients requiring oral or other systemic corticosteroids should be weaned slowly from oral or other systemic corticosteroid use after transferring to QVAR. Lung function (FEV1 or PEF), beta-agonist use, and asthma symptoms should be carefully monitored during withdrawal of oral or other systemic corticosteroids. In addition to monitoring asthma signs and symptoms, patients should be observed for signs and symptoms of adrenal insufficiency such as fatigue, lassitude, weakness, nausea and vomiting, and hypotension.

Transfer of patients from systemic corticosteroid therapy to QVAR may unmask allergic conditions previously suppressed by the systemic corticosteroid therapy, e.g., rhinitis, conjunctivitis, eczema, arthritis, and eosinophilic conditions.

During withdrawal from oral corticosteroids, some patients may experience symptoms of systemically active corticosteroid withdrawal, e.g., joint and/or muscular pain, lassitude, and depression, despite maintenance or even improvement of respiratory function.

5.4 Immunosuppression

Persons who are on drugs which suppress the immune system are more susceptible to infections than healthy individuals. Chickenpox and measles, for example, can have a more serious or even fatal course in non-immune children or adults on corticosteroids. In such children or adults who have not had these diseases or been properly immunized, particular care should be taken to avoid exposure. It is not known how the dose, route and duration of corticosteroid administration affects the risk of developing a disseminated infection. Nor is the contribution of the underlying disease and/or prior corticosteroid treatment known. If exposed to chickenpox, prophylaxis with varicella-zoster immune globulin (VZIG) may be indicated. If exposed to measles, prophylaxis with pooled intramuscular immunoglobulin (IG) may be indicated. (See the respective package inserts for complete VZIG and IG prescribing information.) If chickenpox develops, treatment with antiviral agents may be considered.

Inhaled corticosteroids should be used with caution, if at all, in patients with active or quiescent tuberculosis infection of the respiratory tract; untreated systemic fungal, bacterial, parasitic or viral infections; or ocular herpes simplex.

5.5 Paradoxical Bronchospasm

Inhaled corticosteroids may produce inhalation induced bronchospasm with an immediate increase in wheezing after dosing that may be life-threatening. If inhalation induced bronchospasm occurs following dosing with QVAR, it should be treated immediately with an inhaled, short-acting bronchodilator. Treatment with QVAR should be discontinued and alternate therapy instituted.

5.6 Immediate Hypersensitivity Reactions

Hypersensitivity reactions, such as urticaria, angioedema, rash, and bronchospasm, may occur after administration of QVAR. Discontinue QVAR if such reactions occur [see Contraindications (4.2)]

5.7 Hypercorticism and Adrenal Suppression

QVAR will often help control asthma symptoms with less suppression of HPA function than therapeutically equivalent oral doses of prednisone. Since beclomethasone dipropionate is absorbed into the circulation and can be systemically active at higher doses, the beneficial effects of QVAR in minimizing HPA dysfunction may be expected only when recommended dosages are not exceeded and individual patients are titrated to the lowest effective dose.

Because of the possibility of systemic absorption of inhaled corticosteroids, patients treated with QVAR should be observed carefully for any evidence of systemic corticosteroid effects. Particular care should be taken in observing patients postoperatively or during periods of stress for evidence of inadequate adrenal response.

It is possible that systemic corticosteroid effects such as hypercorticism and adrenal suppression (including adrenal crisis) may appear in a small number of patients, particularly when beclomethasone dipropionate is administered at higher than recommended doses over prolonged periods of time. If such effects occur, the dosage of QVAR should be reduced slowly, consistent with accepted procedures for reducing systemic corticosteroids and for management of asthma symptoms.

5.8 Effects on Growth

Orally inhaled corticosteroids, including QVAR, may cause a reduction in growth velocity when administered to pediatric patients. Monitor the growth of pediatric patients receiving QVAR routinely (e.g., via stadiometry). To minimize the systemic effects of orally inhaled corticosteroids, including QVAR, titrate each patient’s dose to the lowest dosage that effectively controls his/her symptoms [see Use in Specific Populations (8.4)].

5.9 Reduction in Bone Mineral Density

Decreases in bone mineral density (BMD) have been observed with long-term administration of products containing inhaled corticosteroids. The clinical significance of small changes in BMD with regard to long-term outcomes, such as fracture, is unknown. Patients with major risk factors for decreased bone mineral content, such as prolonged immobilization, family history of osteoporosis, or chronic use of drugs that can reduce bone mass (e.g., anticonvulsants and corticosteroids) should be monitored and treated with established standards of care.

5.10 Eye Disorders

Glaucoma, increased intraocular pressure, blurred vision and cataracts have been reported following the use of long-term administration of inhaled corticosteroids. Therefore, close monitoring is warranted in patients with a change in vision or with a history of increased intraocular pressure, blurred vision, glaucoma and/or cataracts while using QVAR.

6 ADVERSE REACTIONS

Systemic and local corticosteroid use may result in the following:

- Candida albicans infection [see Warnings and Precautions (5.1)]
- Immunosuppression [see Warnings and Precautions (5.4)]
- Hypercorticism and adrenal suppression [see Warnings and Precautions (5.7)]
- Growth effects [see Warnings and Precautions (5.8) and Use in Specific Populations (8.4)]
- Eye Disorders [see Warnings and Precautions (5.10)]

6.1 Clinical Trials Experience

Because clinical trials are conducted under widely varying conditions, adverse reaction rates observed in the clinical trials of a drug cannot be directly compared to rates in the clinical trials of another drug and may not reflect the rates observed in practice.

The following reporting rates of common adverse experiences are based upon 4 clinical trials in which 1196 patients (671 female and 525 male adults previously treated with as-needed bronchodilators and/or inhaled corticosteroids) were treated with QVAR (doses of 40, 80, 160, or 320 mcg twice daily) or CFC-BDP (doses of 42, 168, or 336 mcg twice daily) or placebo. Table 1 below includes all events reported by patients taking QVAR (whether considered drug related or not) that occurred at a rate over 3% for QVAR. In considering these data, difference in average duration of exposure and clinical trial design should be taken into account.

Table 1 Adverse Events Reported by at Least 3% of the Patients for QVAR by Treatment and Daily Dose

Adverse Events | Placebo (N=289) % | QVAR
Adverse Events | Placebo (N=289) % | Total (N=624) % | 80-160 mcg (N=233) % | 320 mcg (N=335) % | 640 mcg (N=56) %
Headache | 9 | 12 | 15 | 8 | 25
Pharyngitis | 4 | 8 | 6 | 5 | 27
Upper Respiratory Tract Infection | 11 | 9 | 7 | 11 | 5
Rhinitis | 9 | 6 | 8 | 3 | 7
Increased Asthma Symptoms | 18 | 3 | 2 | 4 | 0
Oral Symptoms Inhalation Route | 2 | 3 | 3 | 3 | 2
Sinusitis | 2 | 3 | 3 | 3 | 0
Pain | <1 | 2 | 1 | 2 | 5
Back Pain | 1 | 1 | 2 | <1 | 4
Dysphonia | 2 | <1 | 1 | 0 | 4

Other adverse events that occurred in these clinical trials using QVAR with an incidence of 1% to 3% and which occurred at a greater incidence than placebo were nausea, dysmenorrhea, and coughing. Oropharyngeal candidiasis occurred in <1% of patients in both QVAR and placebo treatment groups.

Pediatric Studies

In two 12-week placebo-controlled studies in steroid naive pediatric patients 5 to 12 years of age, no clinically relevant differences were found in the pattern, severity, or frequency of adverse events compared with those reported in adults, with the exception of conditions which are more prevalent in a pediatric population generally.

6.2 Postmarketing Experience

In addition to adverse reactions experienced in the clinical trials, the following adverse events have been reported during post-approval use of QVAR. Because they are reported voluntarily from a population of uncertain size, it is not always possible to reliably estimate their frequency or establish a causal relationship to drug exposure.

Local Effects: Localized infections with Candida albicans have occurred in patients treated with QVAR or other orally inhaled corticosteroids [see Warnings and Precautions (5.1)].

Psychiatric and Behavioral Changes: Aggression, depression, sleep disorders, psychomotor hyperactivity, and suicidal ideation have been reported (primarily in children).

Eye Disorders: Blurred vision, central serous chorioretinopathy (CSC).

8 USE IN SPECIFIC POPULATIONS

8.1 Pregnancy

Risk Summary

There are no adequate and well-controlled studies with QVAR or beclomethasone dipropionate in pregnant women. There are clinical considerations with the use of inhaled corticosteroids (ICS), including beclomethasone dipropionate, in pregnant women [see Clinical Considerations]. Also, no published studies, including studies of large birth registries, have to date related the use of ICS to any increases in congenital malformations or other adverse perinatal outcomes. Thus, available human data do not establish the presence or absence of drug-associated risk to the fetus. In animal reproduction studies, beclomethasone dipropionate resulted in adverse developmental effects in mice and rabbits at subcutaneous doses equal to or greater than approximately 0.75 times the maximum recommended human daily inhalation dose (MRHDID) in adults (0.64 mg/day) [see Data]. In rats exposed to beclomethasone dipropionate by inhalation, dose-related gross injury to the fetal adrenal glands was observed at doses greater than 180 times the MRHDID, but there was no evidence of external or skeletal malformations or embryolethality at inhalation doses up to 440 times the MRHDID.

The estimated background risk of major birth defects and miscarriage for the indicated population(s) are unknown. In the US general population, the estimated risk of major birth defects and miscarriage in clinically recognized pregnancies is 2-4% and 15-20%, respectively.

Clinical Considerations

Disease-Associated Maternal and/or Embryofetal Risk

The risk of complications to the mother and developing fetus from inadequate control of asthma must be balanced against the risks from exposure to beclomethasone dipropionate. In women with poorly or moderately controlled asthma, evidence demonstrates that there is an increased risk of preeclampsia in the mother and prematurity, low birth weight and small for gestational age for the neonate. The level of asthma control should be closely monitored in pregnant women and treatment adjusted as necessary to maintain optimal control.

Labor or Delivery

There are no specific human data regarding any adverse effects of inhaled beclomethasone dipropionate on labor and delivery.

Data

Animal Data

In an embryofetal development study in pregnant rats, beclomethasone dipropionate administration during organogenesis from gestation days 6 to 15 at inhaled doses 180 times the MRHDID in adults and higher (on a mg/m^2 basis at maternal doses of 11.5 and 28.3 mg/kg/day) produced dose-dependent gross injury (characterized by red foci) of the adrenal glands in fetuses. There were no findings in the adrenal glands of rat fetuses at an inhaled dose that was 40 times the MRHDID in adults (on a mg/m^2 basis at a maternal dose of 2.4 mg/kg/day). There was no evidence of external or skeletal malformations or embryolethality in rats at inhaled doses up to 440 times the MRHDID (on a mg/m^2 basis at maternal doses up to 28.3 mg/kg/day).

In an embryofetal development study in pregnant mice, beclomethasone dipropionate administration from gestation days 1 to 18 at subcutaneous doses equal to and greater than 0.75 times the MRHDID in adults (on a mg/m^2 basis at maternal doses of 0.1 mg/kg/day and higher) produced adverse developmental effects (increased incidence of cleft palate). A no-effect dose in mice was not identified. In a second embryofetal development study in pregnant mice, beclomethasone dipropionate administration from gestation days 1 to 13 at subcutaneous doses equal to and greater than 2.3 times the MRHDID in adults (on a mg/m^2 basis at a maternal dose of 0.3 mg/kg/day) produced embryolethal effects (increased fetal resorptions) and decreased pup survival.

In an embryofetal development study in pregnant rabbits, beclomethasone dipropionate administration during organogenesis from gestation days 7 to 16 at subcutaneous doses equal to and greater than 0.75 times the MRHDID in adults (on a mg/m^2 basis at maternal doses of 0.025 mg/kg/day and higher) produced external and skeletal malformations and embryolethal effects (increased fetal resorptions). There were no effects in fetuses of pregnant rabbits administered a subcutaneous dose 0.2 times the MRHDID in adults (on a mg/m^2 basis at a maternal dose of 0.006 mg/kg/day).

8.2 Lactation

Risk Summary

There are no data available on the presence of beclomethasone dipropionate in human milk, the effects on the breastfed child, or the effects on milk production. However, other inhaled corticosteroids have been detected in human milk.

The developmental and health benefits of breastfeeding should be considered along with the mother’s clinical need for QVAR and any potential adverse effects on the breastfed child from beclomethasone dipropionate or from the underlying maternal condition.

8.3 Females and Males of Reproductive Potential

Impairment of fertility was observed in rats and dogs at oral doses of beclomethasone dipropionate corresponding to 250 and 25 times the MRHDID for adults on a mg/m^2 basis, respectively [see Nonclinical Toxicology (13.1)].

8.4 Pediatric Use

Eight-hundred and thirty-four children between the ages of 5 and 12 were treated with HFA beclomethasone dipropionate (HFA-BDP) in clinical trials. The safety and effectiveness of QVAR in children below 5 years of age have not been established.

Use of QVAR with a spacer device in children less than 5 years of age is not recommended. In vitro dose characterization studies were performed with QVAR 40 mcg/actuation with the OptiChamber and AeroChamber Plus® spacer utilizing inspiratory flows representative of children under 5 years old. These studies indicated that the amount of medication delivered through the spacing device decreased rapidly with increasing wait times of 5 to 10 seconds as shown in Table 2. If QVAR is used with a spacer device, it is important to inhale immediately.

Based on the average inspiratory flow rates generated by children 6 months to 5 years old, the projected daily dose derived from QVAR 40 mcg at one puff per day at various wait times is depicted in Table 2 below:

Table 2 Average Daily Dose Based on Wait Time in Pediatric Patients

 | Wait time, seconds | Mean medication delivery through AeroChamber mcg/actuation [Summary Report; Pediatric Dose Characterization of QVAR with Spacer; 3M Pharmaceutical Development, July 21, 2004] | Body Weight 50th percentile, kg [CDC Growth charts, developed by the National Center for Health Statistics in collaboration with the National Center for Chronic Disease Prevention and Health Promotion (2000).] | Medication delivered per dose, mcg/kg [Includes an estimated 20% loss in the masks\] , [QVAR 40mcg in an average adult without using a spacer delivers approximately 0.4 mcg/kg, or bid, 0.8 mcg/kg/day.]
Age 6 months, Flow rate 4.8 L/min | 0 | 11.5 | 7.6 | 1.2
Age 2 years, Flow rate 8.2 L/min | 0 | 14.1 | 13.5 | 0.83
Age 2 years, Flow rate 8.2 L/min | 5 | 5.4 | 13.5 | 0.32
Age 2 years, Flow rate 8.2 L/min | 10 | 3.9 | 13.5 | 0.23
Age 5 years, Flow rate 11.0 L/min | 0 | 17.5 | 18 | 0.78

Controlled clinical studies have shown that inhaled corticosteroids may cause a reduction in growth velocity in pediatric patients. A 12-month, randomized, controlled clinical trial evaluated the effects of HFA beclomethasone dipropionate without spacer versus CFC beclomethasone dipropionate with large-volume spacer on growth in children age 5 to 11. A total of 520 patients were enrolled, of whom 394 received HFA-BDP (100 to 400 mcg/day ex-valve) and 126 received CFC-BDP (200 to 800 mcg/day ex-valve). Similar control of asthma was noted in each treatment arm. When comparing results at month 12 to baseline, the mean growth velocity in children treated with HFA-BDP was approximately 0.5 cm/year less than that noted with children treated with CFC-BDP via large-volume spacer. The long-term effects of the reduction in growth velocity associated with orally inhaled corticosteroids, including the impact on final adult height, are unknown. The potential for "catch-up" growth following discontinuation of treatment with orally inhaled corticosteroids has not been adequately studied.

The growth of children and adolescents receiving orally inhaled corticosteroids, including QVAR, should be monitored routinely (e.g., via stadiometry). If a child or adolescent on any corticosteroid appears to have growth suppression, the possibility that he/she is particularly sensitive to this effect should be considered. The potential growth effects of prolonged treatment should be weighed against clinical benefits obtained and the risks associated with alternative therapies. To minimize the systemic effects of orally inhaled corticosteroids, including QVAR, each patient should be titrated to his/her lowest effective dose [see Dosage and Administration (2.2)].

8.5 Geriatric Use

Clinical studies of QVAR did not include sufficient numbers of subjects aged 65 and over to determine whether they respond differently from younger subjects. Other reported clinical experience has not identified differences in responses between the elderly and younger patients. In general, dose selection for an elderly patient should be cautious, usually starting at the low end of the dosing range, reflecting the greater frequency of decreased hepatic, renal, or cardiac function, and of concomitant disease or other drug therapy.

11 DESCRIPTION

The active component of QVAR 40 mcg inhalation aerosol and QVAR 80 mcg inhalation aerosol is beclomethasone dipropionate, USP, a corticosteroid having the chemical name 9-chloro-11ß,17,21-trihydroxy-16ß-methylpregna-1,4-diene-3,20-dione 17,21-dipropionate. Beclomethasone dipropionate (BDP) is a diester of beclomethasone, a synthetic corticosteroid chemically related to dexamethasone. Beclomethasone differs from dexamethasone in having a chlorine at the 9-alpha carbon in place of a fluorine, and in having a 16 beta-methyl group instead of a 16 alpha-methyl group. Beclomethasone dipropionate is a white to creamy white, odorless powder with a molecular formula of C28H37ClO7 and a molecular weight of 521.1. Its chemical structure is:

QVAR is a pressurized, metered-dose aerosol with a dose counter intended for oral inhalation only. Each unit contains a solution of beclomethasone dipropionate in propellant HFA-134a (1,1,1,2 tetrafluoroethane) and ethanol. QVAR 40 mcg delivers 40 mcg of beclomethasone dipropionate from the actuator and 50 mcg from the valve. QVAR 80 mcg delivers 80 mcg of beclomethasone dipropionate from the actuator and 100 mcg from the valve. Both products deliver 50 microliters (59 milligrams) of solution formulation from the valve with each actuation. The 40 mcg canisters and the 80 mcg canisters provide 120 inhalations each. QVAR should be "primed" or actuated twice prior to taking the first dose from a new canister, or when the inhaler has not been used for more than 10 days. Avoid spraying in the eyes or face while priming QVAR. This product does not contain chlorofluorocarbons (CFCs).

12 CLINICAL PHARMACOLOGY

12.1 Mechanism of Action

Beclomethasone dipropionate is a corticosteroid demonstrating potent anti-inflammatory activity. The precise mechanism of corticosteroid action on asthma is not known. Corticosteroids have been shown to have multiple anti-inflammatory effects, inhibiting both inflammatory cells (e.g., mast cells, eosinophils, basophils, lymphocytes, macrophages, and neutrophils) and release of inflammatory mediators (e.g., histamine, eicosanoids, leukotrienes, and cytokines). These anti-inflammatory actions of corticosteroids may contribute to their efficacy in asthma.

Beclomethasone dipropionate is a prodrug that is rapidly activated by hydrolysis to the active monoester, 17 monopropionate (17-BMP). Beclomethasone 17 monopropionate has been shown in vitro to exhibit a binding affinity for the human glucocorticoid receptor which is approximately 13 times that of dexamethasone, 6 times that of triamcinolone acetonide, 1.5 times that of budesonide and 25 times that of beclomethasone dipropionate. The clinical significance of these findings is unknown.

Studies in patients with asthma have shown a favorable ratio between topical anti-inflammatory activity and systemic corticosteroid effects with recommended doses of QVAR.

12.2 Pharmacodynamics

HPA Axis Effects

The effects of QVAR on the hypothalamic-pituitary-adrenal (HPA) axis were studied in 40 corticosteroid-naive patients. QVAR, at doses of 80, 160 or 320 mcg twice daily was compared with placebo and 336 mcg twice daily of beclomethasone dipropionate in a CFC propellant based formulation (CFC-BDP). Active treatment groups showed an expected dose-related reduction in 24-hour urinary-free cortisol (a sensitive marker of adrenal production of cortisol). Patients treated with the highest dose recommended of QVAR (320 mcg twice daily) had a 37.3% reduction in 24-hour urinary-free cortisol compared to a reduction of 47.3% produced by treatment with 336 mcg twice daily of CFC-BDP. There was a 12.2% reduction in 24-hour urinary-free cortisol seen in the group of patients that received 80 mcg twice daily of QVAR and a 24.6% reduction in the group of patients that received 160 mcg twice daily. An open label study of 354 asthma patients given QVAR at recommended doses for one year assessed the effect of QVAR treatment on the HPA axis (as measured by both morning and stimulated plasma cortisol). Less than 1% of patients treated for one year with QVAR had an abnormal response (peak less than 18 mcg/dL) to short-cosyntropin test.

12.3 Pharmacokinetics

Beclomethasone dipropionate (BDP) undergoes rapid and extensive conversion to beclomethasone-17-monopropionate (17-BMP) during absorption. The pharmacokinetics of 17-BMP has been studied in asthmatics given single doses.

Absorption

The mean peak plasma concentration (Cmax) of BDP was 88 pg/ml at 0.5 hour after inhalation of 320 mcg using QVAR (4 actuations of the 80 mcg/actuation strength). The mean peak plasma concentration of the major and most active metabolite, 17-BMP, was 1419 pg/ml at 0.7 hour after inhalation of 320 mcg of QVAR. When the same nominal dose is provided by the two QVAR strengths (40 and 80 mcg/actuation), equivalent systemic pharmacokinetics can be expected. The Cmax of 17-BMP increased dose proportionally in the dose range of 80 and 320 mcg.

Metabolism

Three major metabolites are formed via cytochrome P450-3A catalyzed biotransformation: beclomethasone-17-monopropionate (17-BMP), beclomethasone-21-monopropionate (21-BMP) and beclomethasone (BOH). Lung slices metabolize BDP rapidly to 17-BMP and more slowly to BOH. 17-BMP is the most active metabolite.

Distribution

The in vitro protein binding for 17-BMP was reported to be 94-96% over the concentration range of 1000 to 5000 pg/mL. Protein binding was constant over the concentration range evaluated. There is no evidence of tissue storage of BDP or its metabolites.

Elimination

The major route of elimination of inhaled BDP appears to be via hydrolysis. More than 90% of inhaled BDP is found as 17-BMP in the systemic circulation. The mean elimination half-life of 17-BMP is 2.8 hours. Irrespective of the route of administration (injection, oral or inhalation), BDP and its metabolites are mainly excreted in the feces. Less than 10% of the drug and its metabolites are excreted in the urine.

Special Populations

Formal pharmacokinetic studies using QVAR were not conducted in any special populations.

Pediatrics

The pharmacokinetics of 17-BMP, including dose and strength proportionalities, is similar in children and adults, although the exposure is highly variable. In 17 children (mean age 10 years), the Cmax of 17-BMP was 787 pg/ml at 0.6 hour after inhalation of 160 mcg (4 actuations of the 40 mcg/actuation strength of HFA beclomethasone dipropionate). The systemic exposure to 17-BMP from 160 mcg of HFA-BDP administered without a spacer was comparable to the systemic exposure to 17-BMP from 336 mcg CFC-BDP administered with a large volume spacer in 14 children (mean age 12 years). This implies that approximately twice the systemic exposure to 17-BMP would be expected for comparable mg doses of HFA-BDP without a spacer and CFC-BDP with a large volume spacer.

13 NONCLINICAL TOXICOLOGY

13.1 Carcinogenesis, Mutagenesis, Impairment of Fertility

The carcinogenicity of beclomethasone dipropionate was evaluated in rats which were exposed for a total of 95 weeks, 13 weeks at inhalation doses up to 0.4 mg/kg/day and the remaining 82 weeks at combined oral and inhalation doses up to 2.4 mg/kg/day. There was no evidence of treatment-related increases in the incidence of tumors in this study at the highest dose, which is approximately 37 and 72 times the MRHDID in adults and children, respectively, on a mg/m^2 basis.

Beclomethasone dipropionate did not induce gene mutation in bacterial cells or mammalian Chinese Hamster ovary (CHO) cells in vitro. No significant clastogenic effect was seen in cultured CHO cells in vitro or in the mouse micronucleus test in vivo.

In rats, beclomethasone dipropionate caused decreased conception rates at an oral dose of 16 mg/kg/day (approximately 250 times the MRHDID in adults on a mg/m^2 basis). Impairment of fertility, as evidenced by inhibition of the estrous cycle in dogs, was observed following treatment by the oral route at a dose of 0.5 mg/kg/day (approximately 25 times the MRHDID in adults on a mg/m^2 basis). No inhibition of the estrous cycle in dogs was seen following 12 months of exposure to beclomethasone dipropionate by the inhalation route at an estimated daily dose of 0.33 mg/kg (approximately 17 times the MRHDID in adults on a mg/m^2 basis).

14 CLINICAL STUDIES

Blinded, randomized, parallel, placebo-controlled and active-controlled clinical studies were conducted in 940 adult asthma patients to assess the efficacy and safety of QVAR in the treatment of asthma. Fixed doses ranging from 40 mcg to 160 mcg twice daily were compared to placebo, and doses ranging from 40 mcg to 320 mcg twice daily were compared with doses of 42 mcg to 336 mcg twice daily of an active CFC-BDP comparator. These studies provided information about appropriate dosing through a range of asthma severity. A blinded, randomized, parallel, placebo-controlled study was conducted in 353 pediatric patients (age 5 to 12 years) to assess the efficacy and safety of HFA beclomethasone dipropionate in the treatment of asthma. Fixed doses of 40 mcg and 80 mcg twice daily were compared with placebo in this study. In these adult and pediatric efficacy trials, at the doses studied, measures of pulmonary function [forced expiratory volume in 1 second (FEV1) and morning peak expiratory flow (AM PEF)] and asthma symptoms were significantly improved with QVAR treatment when compared to placebo.

In controlled clinical trials with adult patients not adequately controlled with beta-agonist alone, QVAR was effective at improving asthma control at doses as low as 40 mcg twice daily (80 mcg/day). Comparable asthma control was achieved at lower daily doses of QVAR than with CFC-BDP. Treatment with increasing doses of both QVAR and CFC-BDP generally resulted in increased improvement in FEV1. In this trial the improvement in FEV1 across doses was greater for QVAR than for CFC-BDP, indicating a shift in the dose response curve for QVAR.

14.1 Adult and Adolescent Patients Greater Than 12 Years of Age

Patients not Previously Receiving Corticosteroid Therapy

In a 6-week clinical trial, 270 steroid-naive patients with symptomatic asthma being treated with as-needed beta-agonist bronchodilators, were randomized to receive either 40 mcg twice daily of QVAR, 80 mcg twice daily of QVAR, or placebo. Both doses of QVAR were effective in improving asthma control with significantly greater improvements in FEV1, AM PEF, and asthma symptoms than with placebo. Shown below is the change from baseline in AM PEF during this trial.

A 6-Week Clinical Trial in Patients with Mild to Moderate Asthma Not on Corticosteroid Therapy Prior to Study Entry: Mean Change in AM PEF

In a 6-week clinical trial, 256 patients with symptomatic asthma being treated with as-needed beta-agonist bronchodilators, were randomized to receive either 160 mcg twice-daily of QVAR (delivered as either 40 mcg/actuation or 80 mcg/actuation) or placebo. Treatment with QVAR significantly improved asthma control, as assessed by FEV1, AM PEF, and asthma symptoms, when compared to treatment with placebo. Comparable improvement in AM PEF was seen for patients receiving 160 mcg twice-daily QVAR from the 40 mcg and 80 mcg strength products.

Patients Responsive to a Short Course of Oral Corticosteroids

In another clinical trial, 347 patients with symptomatic asthma, being treated with as-needed inhaled beta-agonist bronchodilators and, in some cases, inhaled corticosteroids, were given a 7 to 12-day course of oral corticosteroids and then randomized to receive either 320 mcg daily of QVAR, 672 mcg of CFC-BDP, or placebo. Patients treated with either QVAR or CFC-BDP had significantly better asthma control, as assessed by AM PEF, FEV1 and asthma symptoms, and fewer study withdrawals due to asthma symptoms, than those treated with placebo over 12 weeks of treatment. A daily dose of 320 mcg QVAR administered in divided doses provided comparable control of AM PEF and FEV1 as 672 mcg of CFC-BDP. Shown below are the mean AM PEF results from this trial.

A 12-Week Clinical Trial in Moderate Symptomatic Patients with Asthma Responding to Oral Corticosteroid Therapy: Mean AM PEF by Study Week

Patients Previously on Inhaled Corticosteroids

In a 6-week clinical trial, 323 patients who exhibited a deterioration in asthma control during an inhaled corticosteroid washout period were randomized to daily treatment with either 40, 160, or 320 mcg twice-daily QVAR or 42, 168 or 336 mcg twice-daily CFC-BDP. Treatment with increasing doses of both QVAR and CFC-BDP resulted in increased improvement in FEV1, FEF25-75% (forced expiratory flow over 25-75% of the vital capacity) and asthma symptoms. Shown below is the change from baseline in FEV1 as percent predicted after 6 weeks of treatment.

A 6-Week Dose Response Clinical Trial in Patients with Inhaled Corticosteroid-Dependent Asthma: Mean Change in FEV1 as Percent of Predicted

14.2 Pediatric Patients 5 to 12 Years of Age

In one 12-week clinical trial, pediatric patients (age 5 to 12 years) with symptomatic asthma (N=353) being treated with as-needed beta-agonist bronchodilators were randomized to receive either 40 mcg or 80 mcg twice daily of HFA beclomethasone dipropionate or placebo. Both doses were effective in improving asthma control with significantly greater improvements in FEV1 (9% and 10% predicted change from baseline at week 12 in FEV1 percent predicted, respectively) than with placebo (4% predicted change).

16 HOW SUPPLIED/STORAGE AND HANDLING

Product: 50090-1342

NDC: 50090-1342-0 120 AEROSOL, METERED in a CANISTER / 1 in a BOX

Product: 50090-3033

NDC: 50090-3033-0 120 AEROSOL, METERED in a CANISTER / 1 in a BOX

17 PATIENT COUNSELING INFORMATION

Advise the patients to read the FDA-approved patient labeling (Patient Information and Instructions for Use).

Risks Associated with Corticosteroid Therapy

- Local Effects: Advise patients that localized infections with Candida albicans have occurred in the mouth and pharynx in some patients. If oropharyngeal candidiasis develops, it should be treated with appropriate local or systemic (i.e., oral) antifungal therapy while still continuing with QVAR therapy, but at times therapy with QVAR may need to be temporarily interrupted under close medical supervision. Rinsing the mouth with water without swallowing after inhalation is advised [see Warnings and Precautions (5.1)].
- Immunosuppression: Warn patients who are on immunosuppressant doses of corticosteroids to avoid exposure to chickenpox or measles and, if exposed, to consult their physician without delay. Inform patients of potential worsening of existing tuberculosis, fungal, bacterial, viral, or parasitic infections, or ocular herpes simplex [see Warnings and Precautions (5.4)].
- Hypercorticism and Adrenal Suppression: Advise patients that QVAR may cause systemic corticosteroid effects of hypercorticism and adrenal suppression. Additionally, instruct patients that deaths due to adrenal insufficiency have occurred during and after transfer from systemic corticosteroids. Patients should taper slowly from systemic corticosteroids if transferring to QVAR [see Warnings and Precautions (5.7)].
- Reduction in Bone Mineral Density: Advise patients who are at an increased risk for decreased BMD that the use of corticosteroids may pose an additional risk and that they should be monitored and, where appropriate, be treated for this condition [see Warnings and Precautions (5.9)].
- Reduced Growth Velocity: Inform patients that orally inhaled corticosteroids, including QVAR, may cause a reduction in growth velocity when administered to pediatric patients. Physicians should closely follow the growth of pediatric patients taking corticosteroids by any route [see Warnings and Precautions (5.8)].
- Eye Disorders: Long-term use of inhaled corticosteroids may increase the risk of some eye problems (glaucoma, cataracts, blurred vision); regular eye examinations should be considered [see Warnings and Precautions (5.10)].

Not for Acute Symptoms

- Advise patients that QVAR is not intended for use in the treatment of acute asthma. Acute asthma symptoms should be treated with an inhaled, short-acting beta-2 agonist such as albuterol. Instruct the patient to contact their healthcare provider immediately if there is any deterioration of their asthma [see Warnings and Precautions (5.2)].

Susceptibility to Infections

- Warn persons who are on immunosuppressant doses of corticosteroids to avoid exposure to chickenpox or measles and, if exposed, to consult their physician without delay. Inform patients of potential worsening of existing tuberculosis, fungal, bacterial, viral, or parasitic infections, or ocular herpes simplex [see Warnings and Precautions (5.4)].

Use Daily for Best Effect

- Advise patients to use QVAR at regular intervals, since its effectiveness depends on regular use. Maximum benefit may not be achieved for 1 week or longer after starting treatment. If symptoms do not improve after 2 weeks of therapy or if the condition worsens, patients should be instructed to contact their physician.

Proper Use and Care of the Inhaler

- Priming: Priming is essential to ensure appropriate beclomethasone dipropionate content in each actuation. Instruct patients to prime the inhaler before using for the first time and in cases where the inhaler has not been used for more than 10 days by releasing two sprays into the air, away from the face.
- Cleaning: For normal hygiene, the mouthpiece of the inhaler should be cleaned weekly with a clean, dry tissue or cloth. DO NOT WASH OR PUT ANY PART OF THE INHALER IN WATER.
- Dose Counter: Inform patients that QVAR has a dose counter attached to the actuator. When the patient receives the inhaler, a black dot will appear in the viewing window until it has been primed 2 times, at which point the total number of actuations will be displayed. The dose counter will count down each time a spray is released. The dose-counter window displays the number of sprays left in the inhaler in units of two (e.g., 120, 118, 116, etc). When the counter displays 20, the color of the numbers will change to red to remind the patient to contact their pharmacist for a refill of medication or consult their physician for a prescription refill. When the dose counter reaches 0, the background will change to solid red. Inform patients to discard the QVAR inhaler when the dose counter displays 0 or after the expiration date on the product, whichever comes first.
- Discontinuing QVAR
- Do not stop QVAR use abruptly. Instruct the patient to contact their healthcare provider immediately if use of QVAR is discontinued.

Rx only

Marketed By:

Teva Respiratory, LLC

Frazer, PA 19355

Developed And Manufactured By:

3M Drug Delivery Systems

Northridge, CA 91324

and/or

3M Health Care, Ltd.

Loughborough, UK

© 2017 Teva Respiratory, LLC

QVAR® is a registered trademark of IVAX LLC, a member of the Teva Group.

United States Patent Nos. 6,446,627 and 9,463,289

OptiChamber is a registered trademark of Respironics Healthscan, Inc. and AeroChamber Plus is a registered trademark of Trudell Medical International Trudell Partnership Holdings Limited and Packard Medical Supply Centre Ltd.

QVA-003

PATIENT INFORMATION

Attention Pharmacist: Detach “Patient Information and Instructions for Use” from package insert and dispense with the product.

Patient Information

QVAR® (Kyu-var)

(beclomethasone dipropionate HFA)

inhalation aerosol

What is QVAR?

QVAR is an inhaled prescription medicine used as a maintenance treatment for the prevention and control of asthma in people 5 years of age and older.

- QVAR is not used to relieve sudden breathing problems.

It is not known if QVAR is safe and effective in children less than 5 years of age.

Who should not use QVAR?

Do not use QVAR:

- to treat sudden severe symptoms of asthma.
- as a rescue inhaler.
- if you are allergic to beclomethasone dipropionate or any of the ingredients in QVAR. See the end of this leaflet for a complete list of ingredients in QVAR.

What should I tell my healthcare provider before using QVAR?

Before using QVAR, tell your healthcare provider about all of your medical conditions, including if you:

- are exposed to chickenpox or measles
- have or have had tuberculosis (TB) or any untreated fungal, bacterial or viral infections, or eye infections caused by herpes.
- have weak bones (osteoporosis).
- have an immune system problem
- have or have had eye problems, such as blurred vision, increased pressure in your eye (glaucoma), or cataracts.
- are pregnant or plan to become pregnant. It is not known if QVAR will harm your unborn baby.
- are breastfeeding or plan to breastfeed. It is not known if QVAR passes into your breast milk. Talk to your healthcare provider about the best way to feed your baby if you use QVAR.

Tell your healthcare provider about all of the medications you take, including prescription and over-the-counter medicines, vitamins, and herbal supplements.

How should I use QVAR?

Read the step-by-step instructions for using QVAR at the end of this Patient Information leaflet.

- Use QVAR exactly as your healthcare provider tells you to. Do not use QVAR more often than it is prescribed.
- Do not change or stop using QVAR or other asthma medicines used to treat your breathing problems unless your healthcare provider tells you to. Your healthcare provider will change your medicines as needed.
- You must use QVAR regularly. It may take 1 to 4 weeks, or longer, after you start using QVAR for your asthma symptoms to get better. Do not stop using QVAR, even if you are feeling better, unless your healthcare provider tells you to.
- QVAR comes in 2 strengths (40 and 80 mcg). Your healthcare provider has prescribed the strength that is best for you. Pay attention to the differences between QVAR and your other inhaled medicines, including their prescribed use and the way they look.
- QVAR does not relieve sudden asthma symptoms. Always have a rescue inhaler with you to treat sudden symptoms. Use your rescue inhaler if you have breathing problems between doses of QVAR. If you do not have a rescue inhaler, call your healthcare provider to have a rescue inhaler prescribed for you.
- Rinse your mouth with water without swallowing after each dose of QVAR. This will help lessen the chance of getting a yeast infection (thrush) in your mouth and throat.
- Do not spray QVAR in your face or eyes. If you accidentally get QVAR in your eyes, rinse your eyes with water and if redness or irritation continues, call your healthcare provider.

What should I avoid while using QVAR?

If you have not had, or have not been vaccinated against, chickenpox or measles, you should stay away from people who are infected.

What are the possible side effects of QVAR?

QVAR may cause serious side effects, including:

- fungal infections (thrush) in your mouth and throat. You may develop a yeast infection (Candida albicans) in your mouth and throat.Tell your healthcare provider if you have any redness or white colored patches in your mouth or throat. Rinse your mouth with water without swallowing after using QVAR to help prevent an infection in your mouth or throat.
- worsening asthma or sudden asthma attacks. You should contact your healthcare provider right away if you do not get relief from your sudden asthma attacks, after using your rescue inhaler, during your treatment with QVAR.
- reduced adrenal function (adrenal insufficiency). Adrenal insufficiency that can lead to death can happen when you stop taking oral corticosteroid medicines and start using inhaled corticosteroid medicines. Adrenal insufficiency can also happen in people who take higher doses of QVAR than recommended over a long period of time. When your body is under stress such as from fever, trauma (such as a car accident), infection, or surgery, adrenal insufficiency can get worse. Signs and symptoms of adrenal insufficiency may include:
- feeling tired or exhausted (fatigue)
- lack of energy
- weakness
- dizziness or feeling faint
- nausea and vomiting
- low blood pressure (hypotension)
- immune system effects and a higher chance for infections. Tell your healthcare provider about any signs or symptoms of infection such as:
  - fever
  - pain
  - body aches
  - chills
  - feeling tired
  - nausea
  - vomiting
- increased wheezing (bronchospasm) right after using QVAR. Always have a rescue inhaler with you to treat sudden wheezing.
- serious allergic reactions. Stop using QVAR and call your healthcare provider or get emergency medical help right away if you get any of the following signs or symptoms of an serious allergic reaction:
  - hives
  - swelling of your lips, tongue, or face
  - rash
  - breathing problems
- slowed growth in children. Children should have their growth checked regularly while using QVAR.
- lower bone density. This may be a problem for people who already have a higher chance for low bone density (osteoporosis).
- eye problems. If you have had glaucoma, cataracts or blurred vision in the past, you should have regular eye exams while using QVAR.

The most common side effects of QVAR include:

- headache
- throat irritation (pharyngitis)
- sinus irritation (sinusitis)

Tell your healthcare provider if you have any side effect that bothers you or that does not go away.

These are not all the possible side effects of QVAR. Ask your healthcare provider or pharmacist for more information.

Call your doctor for medical advice about side effects. You may report side effects to FDA at 1-800-FDA-1088.

How should I store QVAR?

- Store QVAR at room temperature between 68ºF to 77ºF (20ºC to 25ºC).
- Your QVAR canister should only be used with the QVAR actuator. Do not use any other medicines in your QVAR actuator.
- The contents of your QVAR canister are under pressure. Do not puncture the QVAR canister.
- Do not store your QVAR canister near heat or a flame. Temperatures above 120ºF may cause the canister to burst.
- Do not throw your QVAR canister into a fire or incinerator.
- When not in use, store QVAR so that the product rests on the concave end of the canister with the plastic actuator on top.

Keep QVAR and all medicines out of the reach of children.

General information about the safe and effective use of QVAR.

Medicines are sometimes prescribed for purposes other than those listed in a Patient Information leaflet. Do not use QVAR for a condition for which it was not prescribed. Do not give QVAR to other people, even if they have the same symptoms that you have. It may harm them.

You can ask your pharmacist or healthcare provider for information about QVAR that is written for health professionals.

What are the ingredients in QVAR?

Active ingredient: beclomethasone dipropionate

Inactive ingredients: propellant HFA-134a and ethanol

For more information, go to www.QVAR.com or call 1-888-482-9522.

QVAPL-003

Instructions for Use

QVAR (Kyu-var)

(beclomethasone dipropionate HFA)

inhalation aerosol

It is important that you read these instructions before using QVAR.

Correct and regular use of the inhaler will prevent or lessen the severity of asthma attacks.

- Do not use the QVAR actuator with a canister of medicine from any other inhaler.
- Do not use a QVAR canister with an actuator from any other inhaler, including another QVAR inhaler.

The parts of your QVAR:

- There are 2 main parts of your QVAR inhaler including the:
- metal canister that holds the medicine (See Figure A)
- plastic actuator that sprays the medicine from the canister (See Figure A)

- Figure A
- The inhaler has a cap that covers the mouthpiece of the actuator to protect it from dust (See Figure A). The cap should be removed before use.
  - The inhaler comes with a dose counter located on the back of the actuator (See Figure B). The dose counter window will show you the number of actuations (puffs) of medicine remaining in units of 2. The inhaler contains “120” actuations (puffs).

Figure B

- The first time you use QVAR inhaler, the dose counter will show “120” actuations remaining (See Figure B). Each time you press the metal canister, a puff of medicine is released and the dose counter will count down.
- When the dose counter reaches 0, it will continue to show 0 and you should replace your QVAR inhaler.
- The dose counter cannot be reset and is permanently attached to the actuator. Never change the numbers for the dose counter or touch the pin inside the actuator.

Do not remove the metal canister from the plastic actuator.

Before using your QVAR inhaler:

Remove the cap from the mouthpiece of the actuator (See Figure C). Check the mouthpiece for objects before use. Make sure the metal canister is fully inserted into the actuator.

Figure C

Priming your QVAR inhaler:

Before you use your QVAR inhaler for the first time or if you have not used your QVAR Inhaler for more than 10 days, you will need to prime your QVAR Inhaler.

- Before priming, the inhaler will show a black dot in the dose counter window (See Figure D).

Figure D

- Hold the QVAR Inhaler in the upright position and with the mouthpiece pointing away from you.
- Press down on the metal canister 2 times and release 2 actuations (puffs) into the air and away from your face.
- After priming 2 times, the dose counter should read “120.”
  - Your QVAR Inhaler is now ready to use.

Using your QVAR inhaler:

Step 1: Remove the cap from the mouthpiece of the actuator (See Figure C).Check the mouthpiece for objects before use. Make sure the metal canister is fully inserted into the actuator.

- Step 2: Breathe out as fully as you comfortably can. Hold the inhaler in the upright position (See Figure E). Close your lips around the mouthpiece, keeping your tongue below it.

- Figure E
- Step 3: While breathing in deeply and slowly, press down on the metal canister with your finger (See Figure E). When you have finished breathing in, hold your breath as long as you comfortably can (5 to 10 seconds).
- Step 4: Take your finger off the metal canister and remove the inhaler from your mouth. Breathe out gently.

If your healthcare provider has told you to take more than 1 inhalation per dose, repeat steps 1 through 4.

- After using your QVAR inhaler:
- Replace the cap over the mouthpiece right away after use.
- You should rinse your mouth with water without swallowing after you finish using QVAR.
- Clean the mouthpiece of your QVAR inhaler weekly with a clean, dry tissue or cloth.
- Do not wash or put any part of your inhaler in water.

When to replace your QVAR Inhaler:

- It is important that you pay attention to the number of actuations (puffs) left in your QVAR inhaler by reading the dose counter.
- When the dose counter on the actuator reads “20”, the color of the number will change to red and you should refill your prescription or ask your healthcare provider if you need another prescription for QVAR Inhaler.
- When the dose counter reaches “0”, the background color in the dose counter window will change to solid red. Throw away your QVAR inhaler as soon as the dose counter reads “0” or by the expiration date on the QVAR Inhaler package, whichever comes first.
- Do not use QVAR past the expiration date.

This Patient Information and Instructions for Use has been approved by the U.S. Food and Drug Administration.

Marketed By:

Teva Respiratory, LLC

- Frazer, PA 19355

Developed And Manufactured By:

3M Drug Delivery Systems AND/OR 3M Health Care, Ltd.

- Northridge, CA 91324 Loughborough, UK

© 2017 Teva Respiratory, LLC

QVAR is a registered trademark of IVAX LLC, a member of the TEVA Group.

QVAIFU-003

Revised: 09/2017

Storage

Store at 25ºC (77ºF).